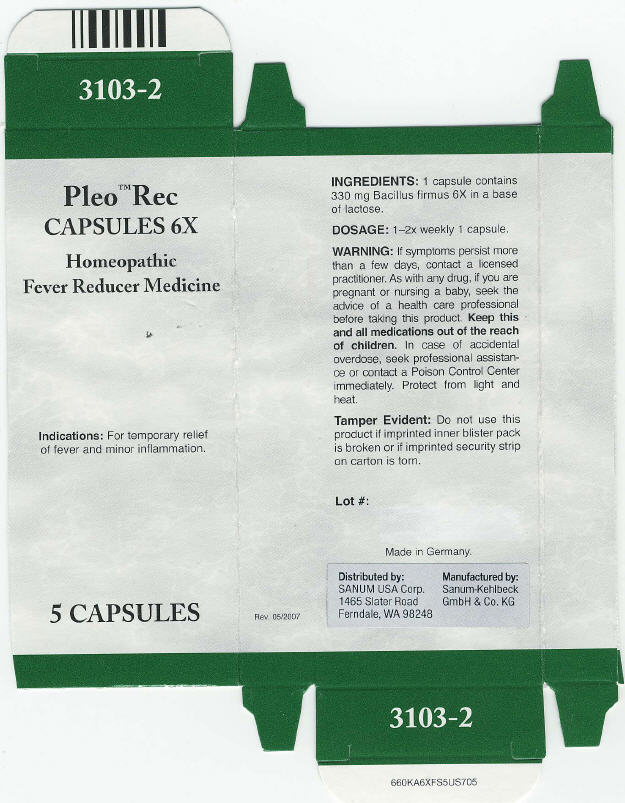 DRUG LABEL: Pleo Rec
NDC: 60681-3103 | Form: CAPSULE
Manufacturer: Sanum Kehlbeck GmbH & Co. KG
Category: homeopathic | Type: HUMAN OTC DRUG LABEL
Date: 20091008

ACTIVE INGREDIENTS: bacillus firmus 6 [hp_X]/1 1
INACTIVE INGREDIENTS: lactose; hypromellose

Pleo™ Rec
CAPSULES 6X

Homeopathic Fever Reducer Medicine

5 CAPSULES

Indications

For temporary relief of fever and minor inflammation.

INGREDIENTS

1 capsule contains: 330 mg Bacillus firmus 6X in a base of lactose.

DOSAGE

1–2x weekly 1 capsule.

WARNING

If symptoms persist more than a few days, contact a licensed practitioner. As with any drug, if you are pregnant or nursing a baby, seek the advice of a health care professional before taking this product. Keep this and all medications out of the reach of children. In case of accidental overdose, seek professional assistance or contact a Poison Control Center immediately. Protect from light and heat.

Tamper Evident

Do not use this product if imprinted inner blister pack is broken or if imprinted security strip on carton is torn.

Made in Germany.

Distributed by:
SANUM USA Corp.
1465 Slater Road
Ferndale, WA 98248

Manufactured by:
Sanum-Kehlbeck
GmbH & Co. KG

Rev. 05/2007

PRINCIPAL DISPLAY PANEL - Capsule Carton

Pleo™ Rec
CAPSULES 4X

Homeopathic
Fever Reducer Medicine

Indications: For temporary relief
of fever and minor inflammation.

5 CAPSULES